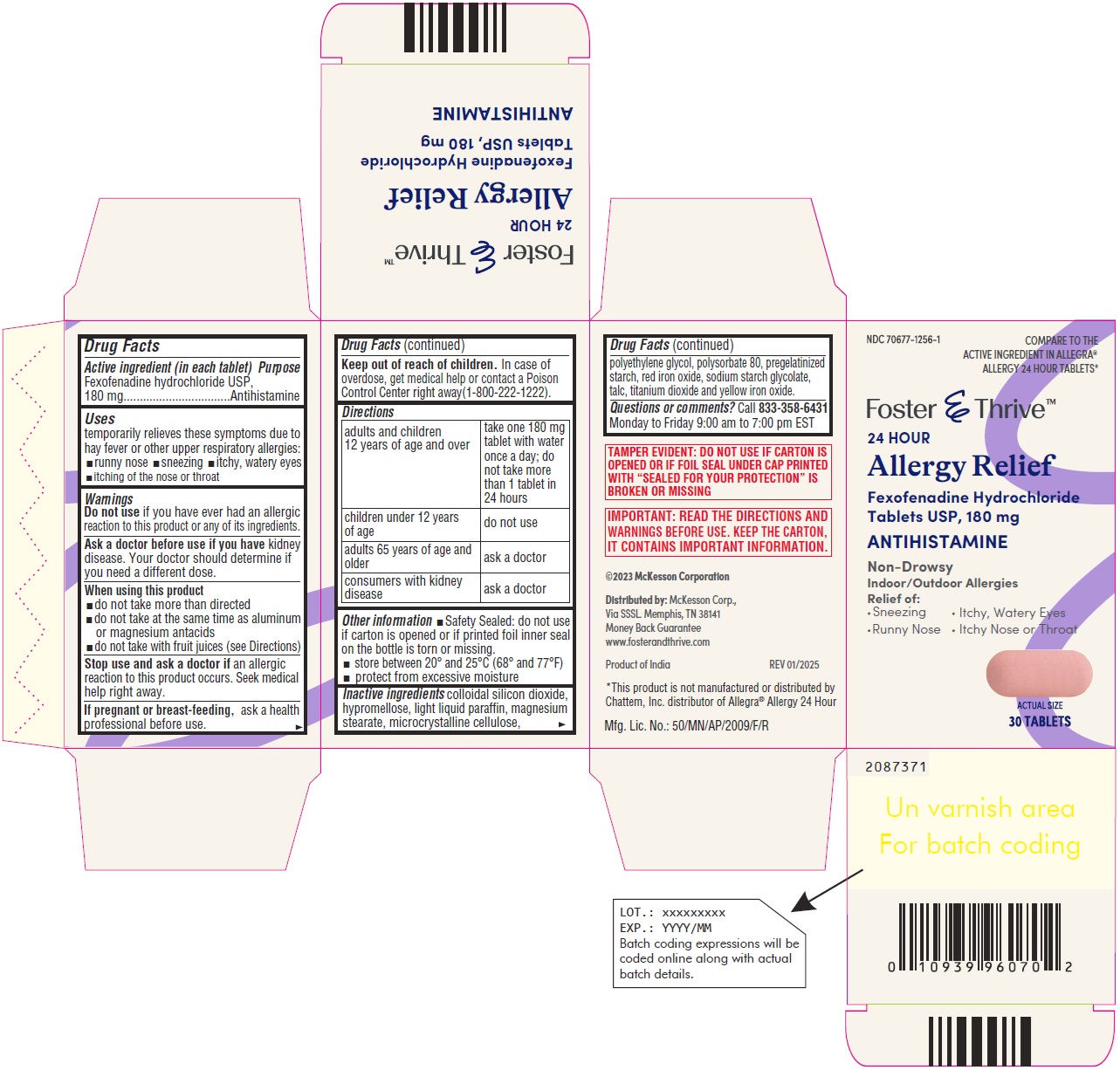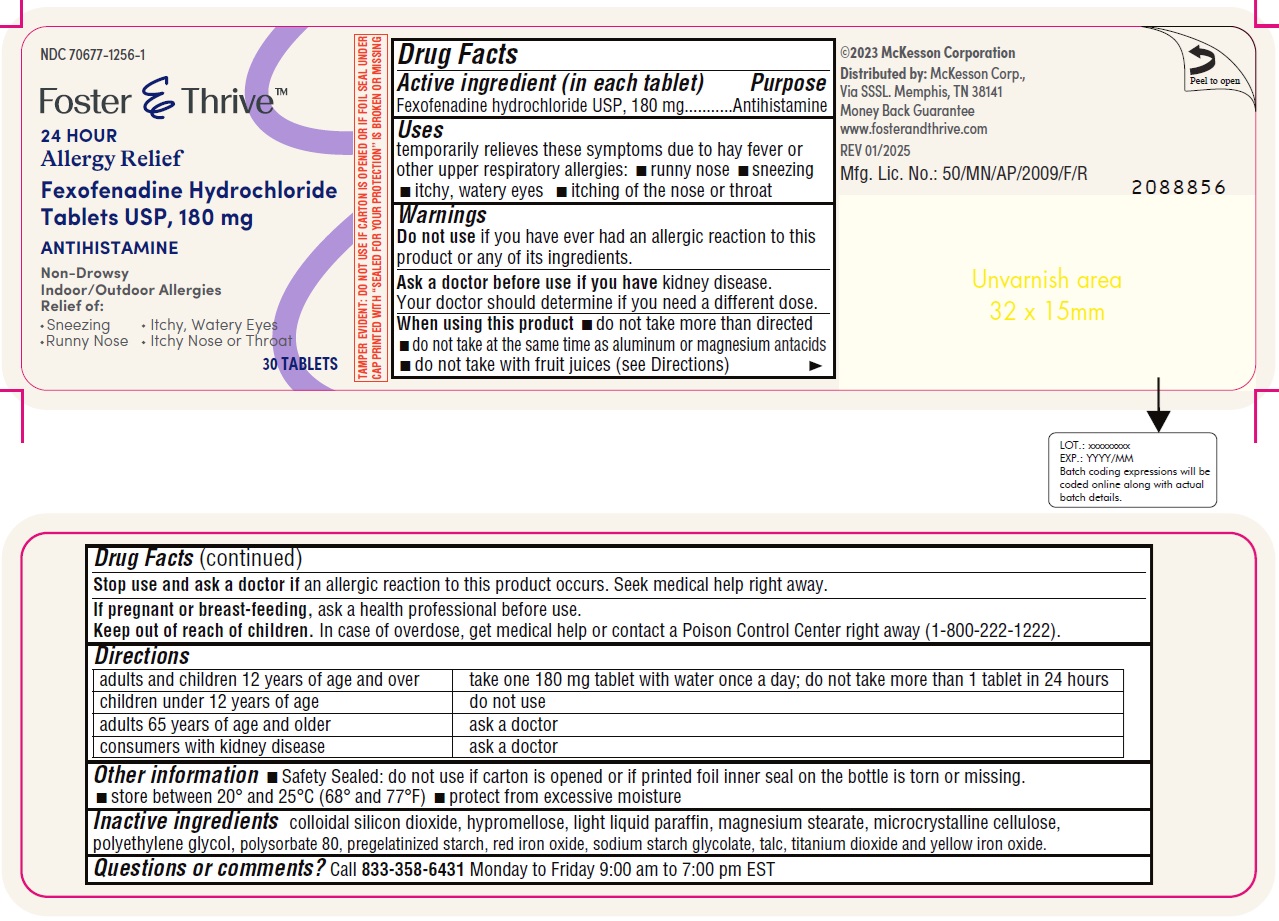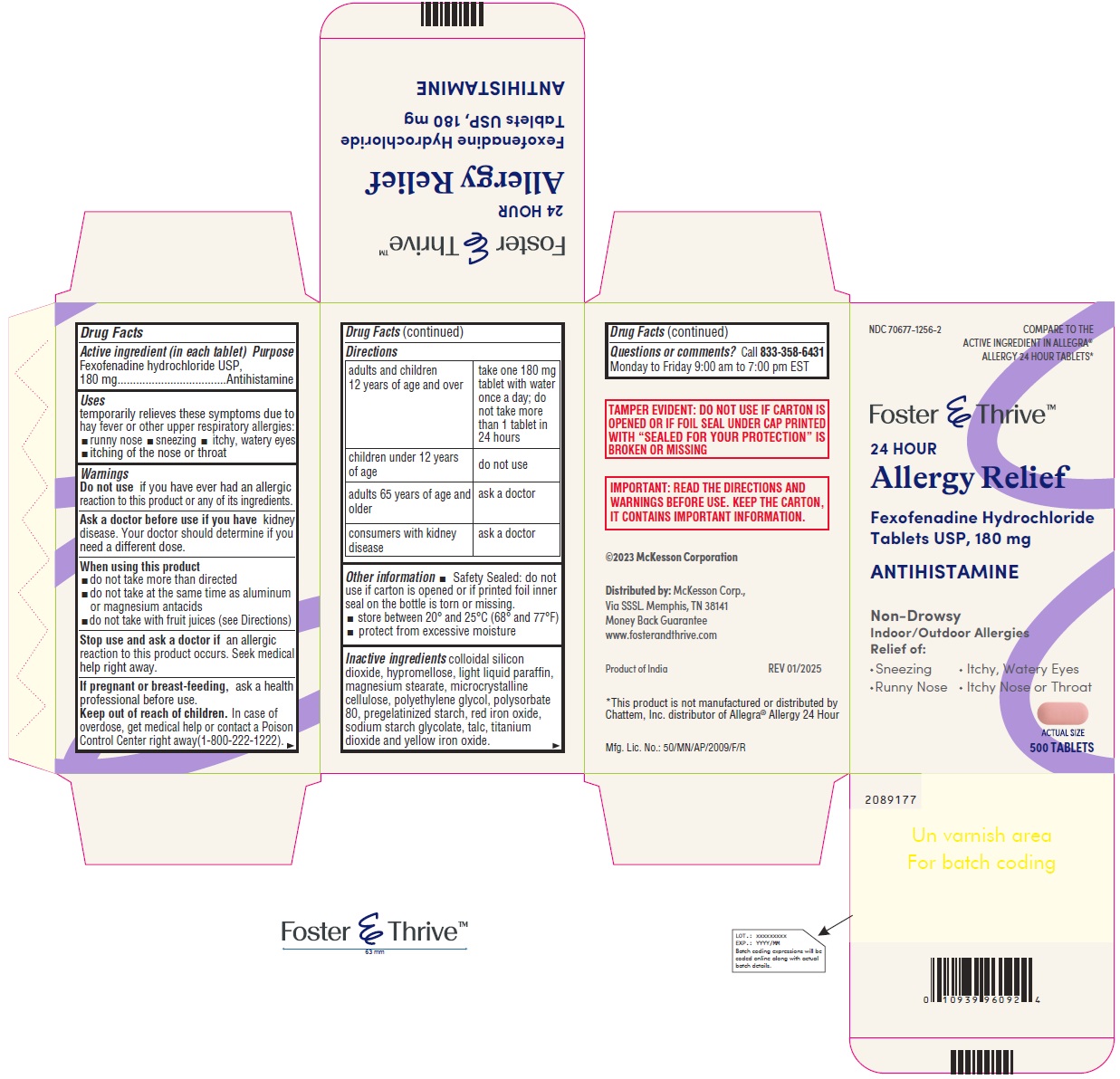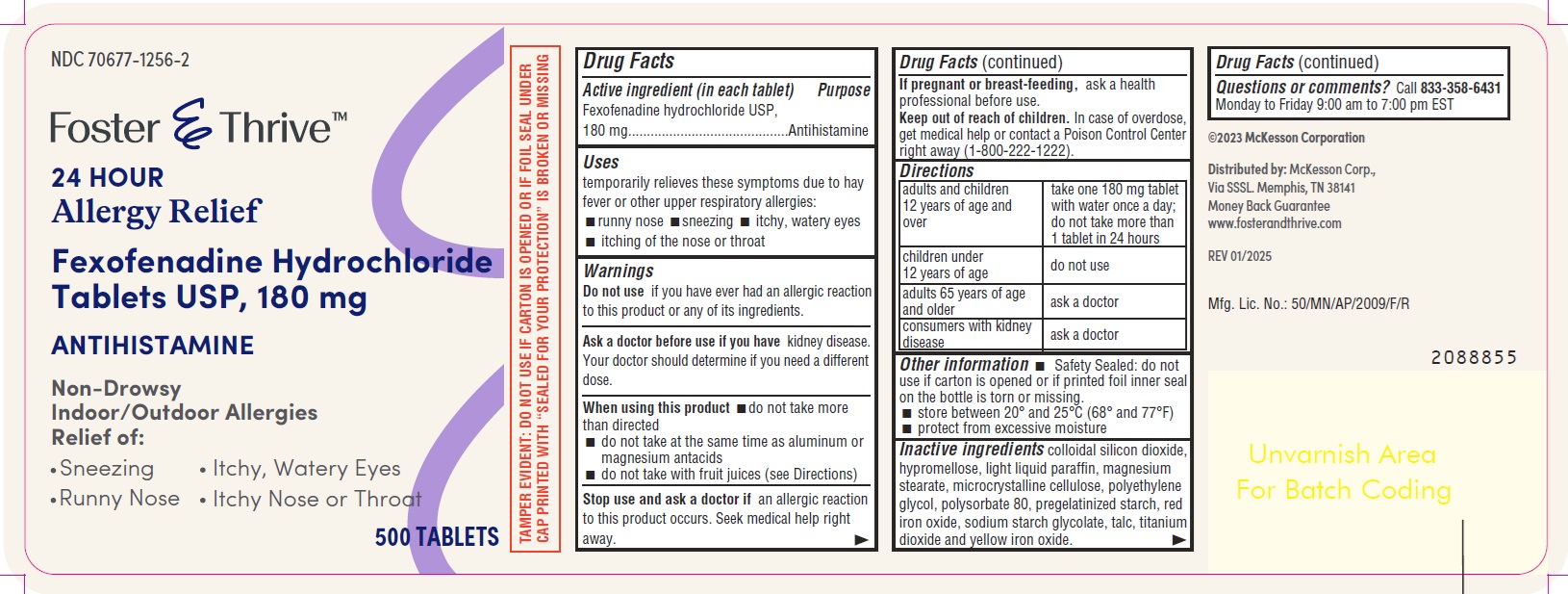 DRUG LABEL: Fexofenadine HCL

NDC: 70677-1256 | Form: TABLET
Manufacturer: Strategic Sourcing Services
Category: otc | Type: HUMAN OTC DRUG LABEL
Date: 20250324

ACTIVE INGREDIENTS: FEXOFENADINE HYDROCHLORIDE 180 mg/1 1
INACTIVE INGREDIENTS: SILICON DIOXIDE; HYPROMELLOSE 2910 (6 MPA.S); LIGHT MINERAL OIL; MAGNESIUM STEARATE; MICROCRYSTALLINE CELLULOSE; POLYSORBATE 80; STARCH, CORN; FERRIC OXIDE RED; FERRIC OXIDE YELLOW; SODIUM STARCH GLYCOLATE TYPE A POTATO; TALC; TITANIUM DIOXIDE; POLYETHYLENE GLYCOL 6000

Fexofenadine Hydrochloride Tablets USP, 180 mg

ACTIVE INGREDIENT(S) in each tablet

Fexofenadine hydrochloride USP, 180 mg

PURPOSE

Antihistamine

USES

temporarily relieves these symptoms due to hay fever or other upper respiratory allergies:

- runny nose
- sneezing
- itchy, watery eyes
- itching of the nose or throat

DO NOT USE

if you have ever had an allergic reaction to this product or any of its ingredients.

ASK A DOCTOR BEFORE USE IF YOU HAVE

Kidney disease. Your doctor should determine if you need a different dose.

WHEN USING THIS PRODUCT

- do not take more than directed
- do not take at the same time as aluminum or magnesium antacids
- do not take with fruit juices (see Directions)

STOP USE AND ASK A DOCTOR IF

an allergic reaction to this product occurs. Seek medical help right away.
If pregnant or breast-feeding,ask a health professional before use.

KEEP OUT OF REACH OF CHILDREN

In case of overdose, get medical help or contact a Poison Control Center right away (1-800-222-1222).

DIRECTIONS

adults and children 12 years of age and over | take one 180 mg tablet with water once a day; do not take more than 1 tablet in 24 hours
children under 12 years of age | do not use
adults 65 years of age and older | ask a doctor
consumers with kidney disease | ask a doctor

OTHER INFORMATION

- Safety Sealed: do not use if carton is opened or if printed foil inner seal on the bottle is torn or missing.
- store between 20° and 25°C (68° and 77°F)
- protect from excessive moisture

INACTIVE INGREDIENTS

colloidal silicon dioxide, hypromellose, light liquid paraffin, magnesium stearate, microcrystalline cellulose, polyethylene glycol, polysorbate 80, pregelatinized starch, red iron oxide, sodium starch glycolate, talc, titanium dioxide and yellow iron oxide.

QUESTIONS OR COMMENTS

Call 833-358-6431Monday to Friday 9:00 am to 7:00 pm EST

PRINCIPAL DISPLAY PANEL

Fexofenadine Hydrochloride Tablets, USP 180 mg 30s Container Label

Fexofenadine Hydrochloride Tablets, USP 180 mg 30s Carton Label

Fexofenadine Hydrochloride Tablets, USP 180 mg 500s Container Label

Fexofenadine Hydrochloride Tablets, USP 180 mg 500s Carton Label